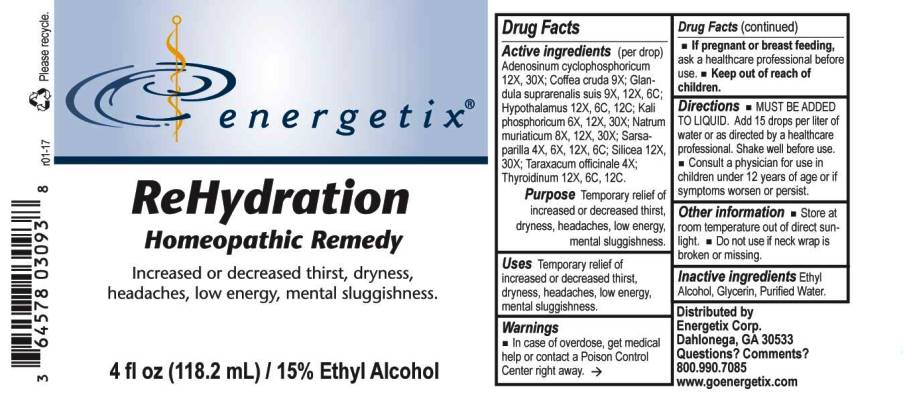 DRUG LABEL: ReHydration
NDC: 64578-0090 | Form: LIQUID
Manufacturer: Energetix Corp
Category: homeopathic | Type: HUMAN OTC DRUG LABEL
Date: 20170131

ACTIVE INGREDIENTS: ADENOSINE CYCLIC PHOSPHATE 12 [hp_X]/1 mL; ARABICA COFFEE BEAN 9 [hp_X]/1 mL; SUS SCROFA ADRENAL GLAND 9 [hp_X]/1 mL; BOS TAURUS HYPOTHALAMUS 12 [hp_X]/1 mL; POTASSIUM PHOSPHATE, DIBASIC 6 [hp_X]/1 mL; SODIUM CHLORIDE 8 [hp_X]/1 mL; SARSAPARILLA 4 [hp_X]/1 mL; SILICON DIOXIDE 12 1/1 mL; TARAXACUM OFFICINALE 4 [hp_X]/1 mL; THYROID, BOVINE 12 [hp_X]/1 mL
INACTIVE INGREDIENTS: WATER; GLYCERIN; ALCOHOL

Drug Facts:

ACTIVE INGREDIENTS:

Adenosinum Cyclophosphoricum 12X, 30X; Coffea Cruda 9X; Glandula Suprarenalis Suis 9X, 12X ,6C; Hypothalamus (Bovine) 12X, 6C, 12C; Kali Phosphoricum 6X, 12X, 30X; Natrum Muriaticum 8X, 12X, 30X; Sarsaparilla 4X, 6X, 12X, 6C; Silicea 12X, 30X; Taraxacum Officinale 4X; Thyroidinum (Bovine) 12X, 6C, 12C.

PURPOSE:

Temporary relief of increased or decreased thirst, dryness, headaches, low energy, mental sluggishness.

WARNINGS:

In case of overdose, get medical help or call a Poison Control Center right away.

If pregnant or breast-feeding, ask a health professional before use.

Keep out of reach of children.

Other Information

Store in cool, dry place out of direct sunlight.

Do not use if neck wrap is broken or missing.

Keep out of reach of children. In case of overdose, contact physician or Poison Control Center right away.

DIRECTIONS:

MUST BE ADDED TO LIQUID. Add 15 drops per liter of water or as directed by a healthcare professional.

Shake well before use.

Consult a physician for use in children under 12 years of age.

USES:

Temporary relief of increased or decreased thirst, dryness, headaches, low energy, mental sluggishness.

INACTIVE INGREDIENTS:

Ethyl Alcohol, Glycerin, Purified Water.

QUESTIONS:

Distributed by
Energetix Corp
Dahlonega, GA 30533
Questions? Comments?
800.990.7085
www.goenergetix.com

PACKAGE LABEL DISPLAY:

energetix

ReHydration

Homeopathic Remedy

Increased or decreased thirst, dryness,
headaches, low energy, mental sluggishness.

2 fl oz (59.1 mL)